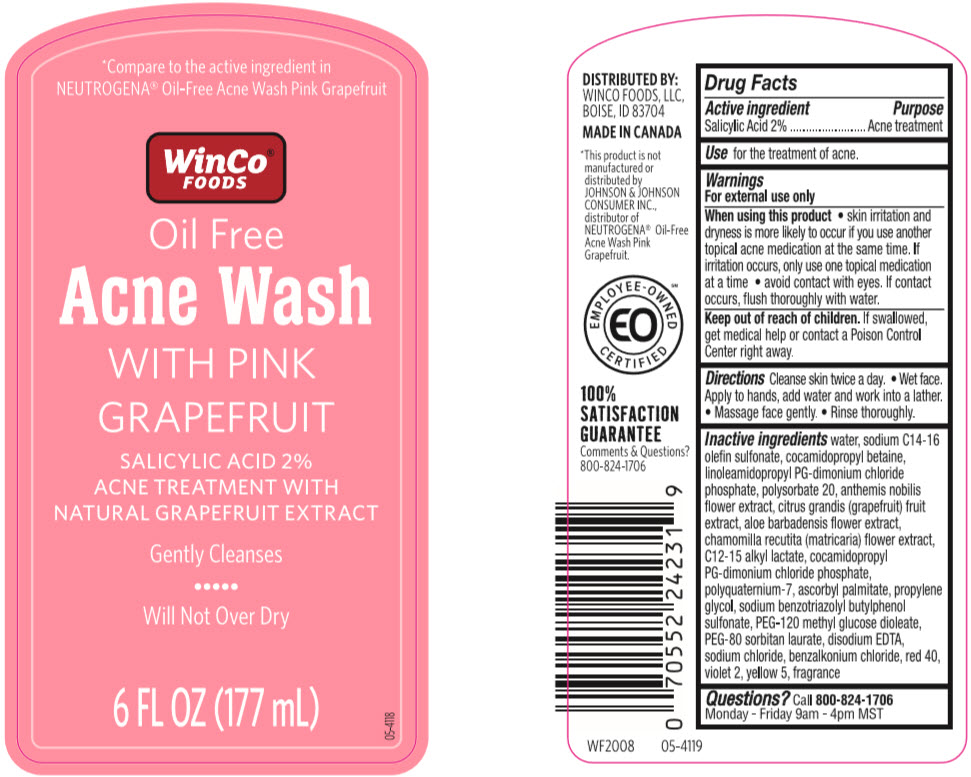 DRUG LABEL: WinCo Foods Oil Free Acne Wash with Pink Grapefruit
NDC: 67091-372 | Form: LOTION
Manufacturer: WINCO FOODS, LLC
Category: otc | Type: HUMAN OTC DRUG LABEL
Date: 20241111

ACTIVE INGREDIENTS: Salicylic Acid 20 mg/1 mL
INACTIVE INGREDIENTS: Water; Sodium C14-16 Olefin Sulfonate; Cocamidopropyl Betaine; LINOLEAMIDOPROPYL PROPYLENE GLYCOL-DIMONIUM CHLORIDE PHOSPHATE; Polysorbate 20; CHAMAEMELUM NOBILE FLOWER; PUMMELO; ALOE VERA FLOWER; CHAMOMILE; C12-15 Alkyl Lactate; COCAMIDOPROPYL PROPYLENE GLYCOL-DIMONIUM CHLORIDE PHOSPHATE; POLYQUATERNIUM-7 (70/30 ACRYLAMIDE/DADMAC; 1600000 MW); Ascorbyl Palmitate; Propylene Glycol; Sodium Benzotriazolyl Butylphenol Sulfonate; PEG-120 Methyl Glucose Dioleate; PEG-80 Sorbitan Laurate; EDETATE DISODIUM; Sodium Chloride; Benzalkonium Chloride; FD&C RED NO. 40; D&C VIOLET NO. 2; FD&C YELLOW NO. 5

WinCo® Foods Oil Free Acne Wash with Pink Grapefruit
Acne treatment

Drug Facts

Active ingredient

Salicylic Acid 2%

Purpose

Acne treatment

Use

For the treatment of acne.

Warnings

For external use only

When using this product

- skin irritation and dryness is more likely to occur if you use another topical acne medication at the same time. If irritation occurs, only use one topical medication at a time
- avoid contact with eyes. If contact occurs, flush thoroughly with water.

Keep out of reach of children. If swallowed, get medical help or contact a Poison Control Center right away.

Directions

Cleanse skin twice a day

- Wet face. Apply to hands, add water and work into a lather.
- Massage face gently.
- Rinse thoroughly.

Inactive ingredients

Water, Sodium C14-16 Olefin Sulfonate, Cocamidopropyl Betaine, Linoleamidopropyl PG-Dimonium Chloride Phosphate, Polysorbate 20, Anthemis Nobilis Flower Extract, Citrus Grandis (Grapefruit) Fruit Extract, Aloe Barbadensis Flower Extract, Chamomilla Recutita (Matriarca) Flower Extract, C12-15 Alkyl Lactate, Cocamidopropyl PG-diamonium Chloride Phosphate, Polyquaternium-7, Ascorbyl Palmitate, Propylene Glycol, Sodium Benzotriazolyl Butylphenol Sulfonate, PEG-120 Methyl Glucose Dioleate, PG-80 Sorbitan Laurate, Disodium EDTA, Sodium Chloride, Benzalkonium Chloride, Red 40, Violet 2, Yellow5, Fragrance

Questions?

Call 800-824-1706
Monday-Friday 9am -4pm MST

DISTRIBUTED BY:
WINCO FOODS, LLC,
BOISE, ID 83704

PRINCIPAL DISPLAY PANEL - 177 mL Bottle Label

*Compare to the active ingredient in
NEUTROGENA® Oil-Free Acne Wash Pink Grapefruit

WinCo®
FOODS

Oil Free
Acne Wash
WITH PINK
GRAPEFRUIT

SALICYLIC ACID 2%
ACNE TREATMENT WITH
NATURAL GRAPEFRUIT EXTRACT

Gently Cleanses

Will Not Over Dry

6 FL OZ (177 mL)

05-4118